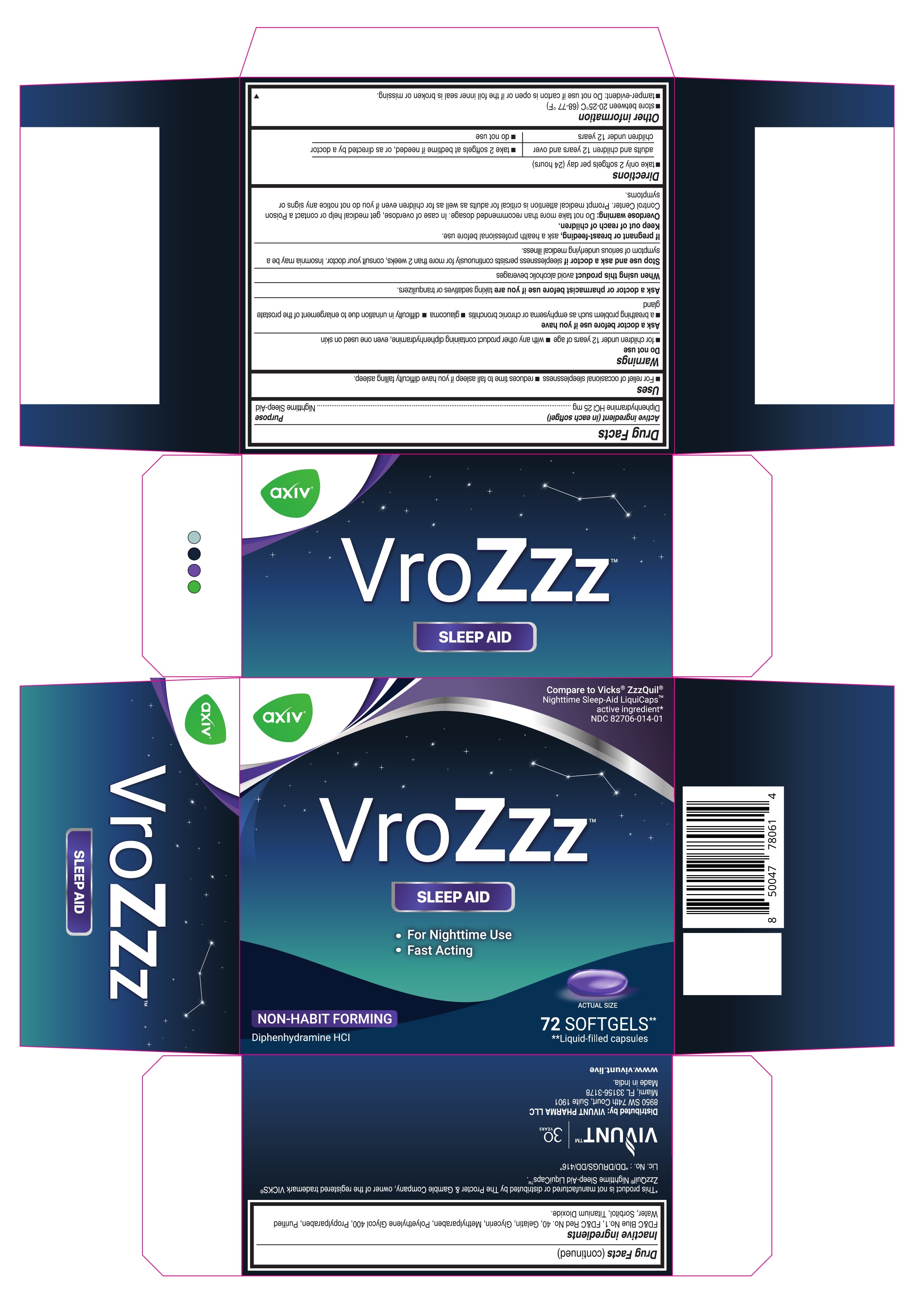 DRUG LABEL: AXIV - VroZzz
NDC: 82706-014 | Form: CAPSULE, LIQUID FILLED
Manufacturer: Vivunt Pharma LLC
Category: otc | Type: HUMAN OTC DRUG LABEL
Date: 20250917

ACTIVE INGREDIENTS: DIPHENHYDRAMINE HYDROCHLORIDE 25 mg/1 1
INACTIVE INGREDIENTS: FD&C BLUE NO. 1; FD&C RED NO. 40; GELATIN; GLYCERIN; METHYLPARABEN; POLYETHYLENE GLYCOL 400; PROPYLPARABEN; WATER; SORBITOL; TITANIUM DIOXIDE

AXIV VroZzz - Softgels

Drug Facts

ACTIVE INGREDIENT

Diphenhydramine HCl

Active Ingredient (in each softgel) | Purpose
Diphenhydramine HCl 25 mg | Nighttime Sleep-Aid

Uses

- For the relief of occasional sleeplessness
- reduces time to fall asleep if you have difficulty falling asleep

Warnings

Do not use

- for children under 12 years of age
- with any other product containing diphenhydramine, even one used on skin

Ask a doctor before use if you have

- a breathing problem such as emphysema or chronic bronchitis
- glaucoma
- difficulty in urination due to enlargement of the prostate gland

Ask a doctor or pharmacist before use if you are

taking sedatives or tranquilizers

When using this product

avoid alcoholic beverages

Stop use and ask a doctor if

sleeplessness persists continuously for more than 2 weeks, consult your doctor. Insomnia may be a symptom of a serious underlying medical illness.

If pregnant or breast-feeding,

ask a health professional before use.

Keep out of reach of children

Overdose warning

Do not take more than recommended dosage. In case of overdose, get medical help or contact a Poison Control Center. Prompt medical attention is critical for adults as well as for children even if you do not notice any signs or symptoms.

Directions

- take only 2 softgels per day (24 hours)

adults & children 12 years and over | take 2 softgels at bedtime if needed, or as directed by a doctor
children under 12 years | do not use

Other information

- store between 20-25°C (68-77 °F)
- tamper-evident: Do not use if carton is open or if the foil inner seal is broken or missing.

Inactive ingredients

FD&C Blue No. 1, FD&C Red No. 40, Gelatin, Glycerin, Methylparaben, Polyethylene Glycol 400, Propylparaben, Purified Water, Sorbitol, Titanium Dioxide.

This product is not manufactured or distributed by The Procter & Gamble Company, owner of the registered trademark VICKS® ZzzQuil® Nighttime Sleep-Aid LiquidCaps™.

Lic. No.: "DD/DRUGS/DD/416"

Distributed by: Vivunt Pharma LLC

8590 w 74TH Court, Suite 1901

Miami, FL 33156-3178

Made in India

www.vivunt.live

PRINCIPAL DISPLAY PANEL

Compare to VICKS® ZzzQuil®

Nighttime Sleep-Aid LiquidCaps™ active ingredient*

NDC 82706-014-01

AXIV - VroZzz

Sleep Aid

For Nighttime Use

Fast Acting

Non-Habit Forming

Diphenhydramine HCl

72 Softgels** **Liquid-filled capsules